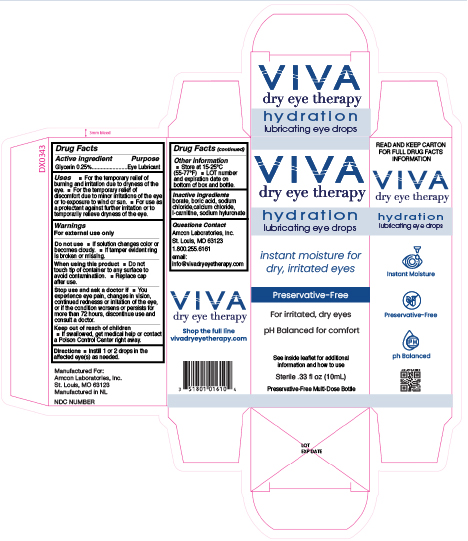 DRUG LABEL: Viva Hydration Boost
NDC: 51801-016 | Form: SOLUTION/ DROPS
Manufacturer: Nomax Inc
Category: otc | Type: HUMAN OTC DRUG LABEL
Date: 20260210

ACTIVE INGREDIENTS: GLYCERIN 2.5 mg/1 mL
INACTIVE INGREDIENTS: LEVOCARNITINE; HYALURONATE SODIUM; SODIUM CHLORIDE; CALCIUM CHLORIDE; BORIC ACID; SODIUM BORATE

ACTIVE INGREDIENT

Glycerin 0.25%

PURPOSE

Lubricant

INDICATIONS AND USAGE

- for the temporary relief of burning and irritation due to dryness of the eye
- for the temporary relief of discomfort due to minor irritations of the eye or to the exposure to wind or sun
- for use as a protectant against further irritation or to temporarily relieve dryness of the eye

WARNINGS

For external use only

DO NOT USE

- if solution changes color or becomes cloudy
- if tamper evident ring is broken or missing

WHEN USING

- do not touch tip of container to any surface to avoid contamination
- replace cap after use

STOP USE

IF

- you experience eye pain, changes in vision, continued redness or irritation of the eye, or if the condition worsens or persists for more than 72 hours, discontinue use and consult a doctor

KEEP OUT OF REACH OF CHILDREN

- if swallowed, get medical help or contact a Poison Control Center right away

INSTRUCTIONS FOR USE

- instill 1 or 2 drops in the affected eye(s) as needed

STORAGE AND HANDLING

- Store at 15-25ºC (55-77ºF)
- LOT number and expiration date on bottom of box and bottle

INACTIVE INGREDIENT

borate, boric acid, sodium chloride, calcium chloride, l-carnitine, sodium hyluronate

QUESTIONS

Amcon Laboratories, Inc.

St. Louis, MO 63123

1.800.255.6161

email:

info@vivadryeyetherapy.com

DOSAGE AND ADMINISTRATION

Glycerin 0.25%

Instill 1 or 2 drops in the affected eye(s) as needed

PACKAGE LABEL

VIVA

dry eye therapy

hydration

lubricating eye drops

instant, moisture for dry, irritated eyes

Preservative-Free

For irritated, dry eyes

pH Balanced for comfort

See inside leaflet for additional information and how to use

Sterile .33 fl oz (10mL)

Preservative-Free Multi-Dose Bottle